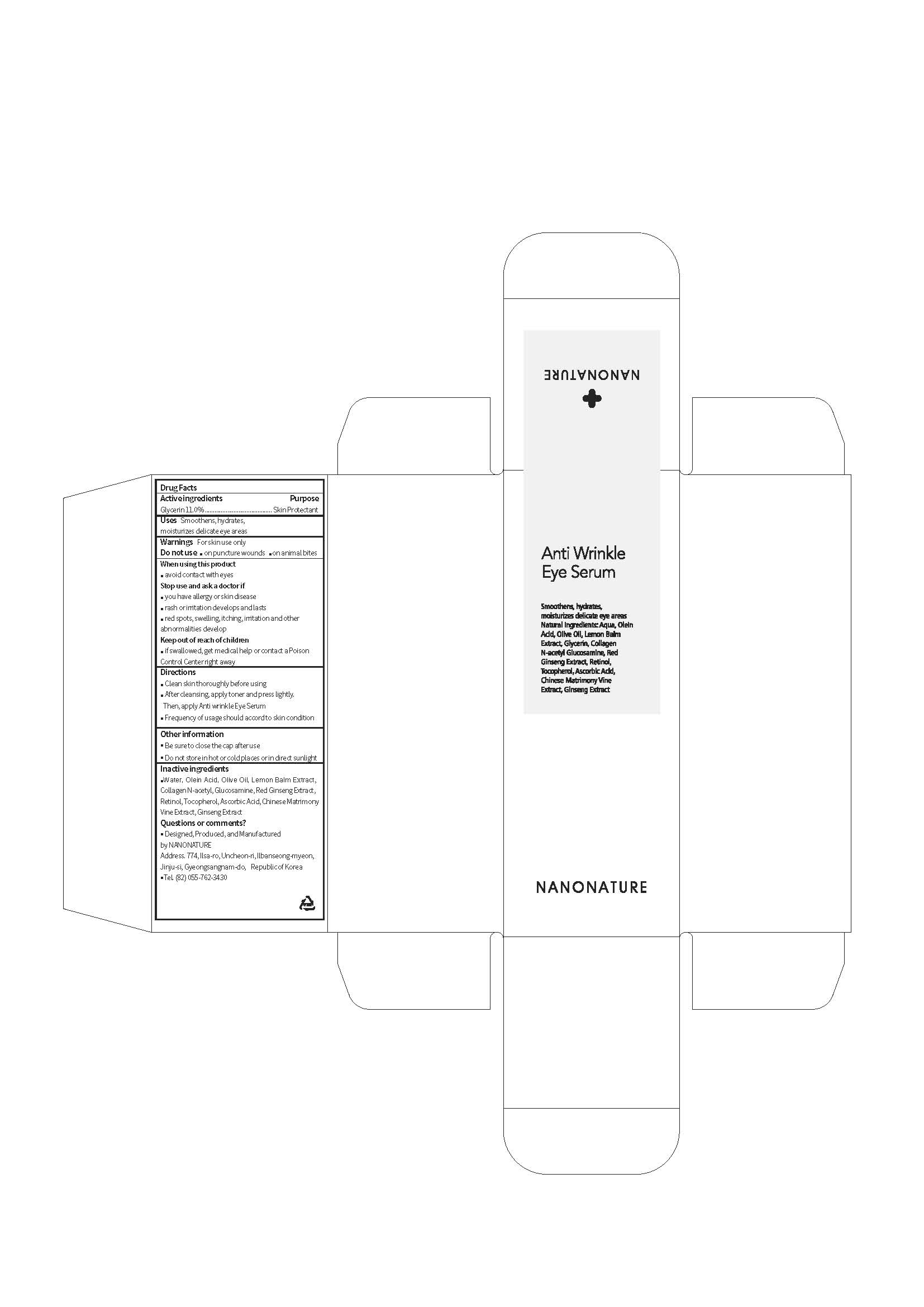 DRUG LABEL: Anti Wrinkle Eye Serum
NDC: 71538-004 | Form: SOLUTION
Manufacturer: NANONATURE
Category: otc | Type: HUMAN OTC DRUG LABEL
Date: 20170717

ACTIVE INGREDIENTS: Glycerin 1.65 g/120 mL
INACTIVE INGREDIENTS: Water; Olive Oil; Tocopherol

ACTIVE INGREDIENT

Glycerin (11.0%) - Skin Protectant

INACTIVE INGREDIENT

Water, Olein Acid, Olive Oil, Lemon Balm Extract, Collagen, N-acetyl Glucosamine, Retinol, Red Ginseng Extract, Retinol, Tocopherol, Ascobic Acid, Chinese Matrimony Vine Extract, Ginseng Extract

PURPOSE

Skin Protectant

WARNINGS

When using this product
 avoid contact with eyes
Stop use and ask a doctor if
 you have allergy or skin disease
 rash or irritation develops and lasts
 red spots, swelling, itching, irritation and other abnormalities develops

KEEP OUT OF REACH OF CHILDREN

 if swallowed, get medical help or contact a Poison Control Center right away

INDICATIONS & USAGE

 Clean skin thoroughly before using
 After cleansing, apply toner and press lightly. Then, apply Anti wrinkle Eye Serum
 Frequency of usage should accord to skin condition

DOSAGE & ADMINISTRATION

 Clean skin thoroughly before using
 After cleansing, apply toner and press lightly. Then, apply Anti wrinkle Eye Serum
 Frequency of usage should accord to skin condition